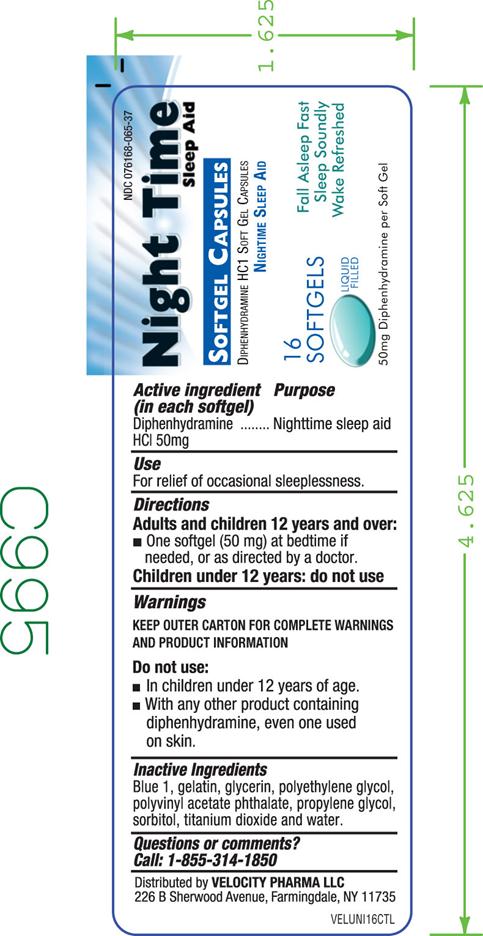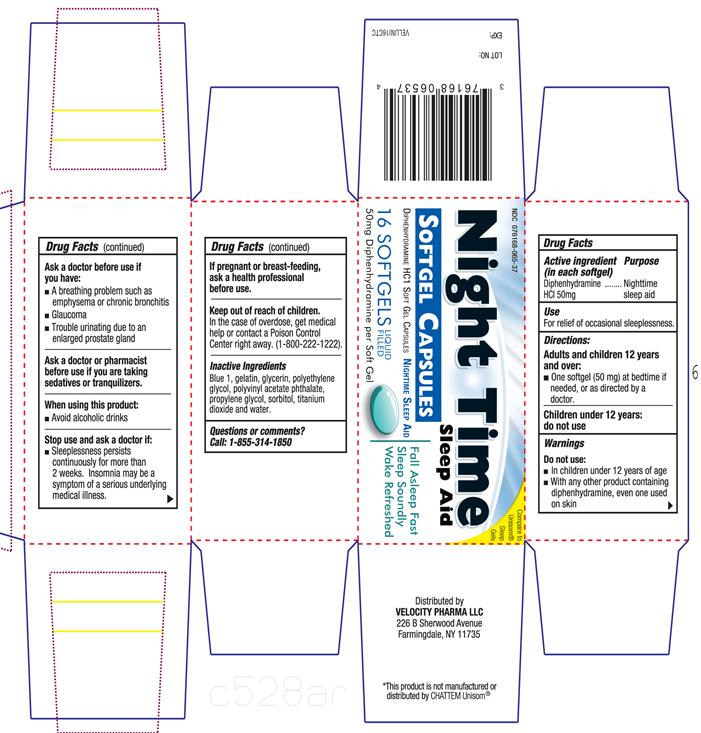 DRUG LABEL: Nightime Sleep Aid
NDC: 76168-065 | Form: CAPSULE, LIQUID FILLED
Manufacturer: Velocity Pharma
Category: otc | Type: HUMAN OTC DRUG LABEL
Date: 20180521

ACTIVE INGREDIENTS: DIPHENHYDRAMINE HYDROCHLORIDE 50 mg/1 1
INACTIVE INGREDIENTS: FD&C BLUE NO. 1; GELATIN; GLYCERIN; POLYETHYLENE GLYCOL 1000; SORBITOL; POLYVINYL ACETATE PHTHALATE; PROPYLENE GLYCOL; TITANIUM DIOXIDE

DIPHENHYDRAMINE HCl 50mg, USP

Active Ingredient

(in each softgel)

Diphenhydramine HCl 50 mg

Purpose

Nighttime sleep aid

Uses

- For relief of occasional sleeplessness.

Directions

- adults and children 12 years and over : one softgel (50 mg) at bed time if needed or as directed by a doctor.
- children under 12 years: do not use

Warnings

Do not use

- in children under 12 years of age.
- with any other product containing diphenhydramine, even one used on skin
  Ask a doctor before use if you have
- glaucoma
- trouble urinating due to an enlarged prostate gland
- a breathing problem such as emphysema or chronic bronchitis
  Ask a doctor or pharmacist before use if you are taking sedatives or tranquilizers
  When using this product
- avoid alcoholic drinks
  If pregnant or breast-feeding, ask a health professional before use.

Keep out of reach of children.

In case of overdose, get medical help or contact a Poison Control Center right away. (1-800-222-1222)

Other Information

- save carton for full directions and warnings

Inactive Ingredients

Blue 1, gelatin, glycerin, polyethylene glycol, polyvinyl acetate phthalate, propylene glycol, sorbitol, titanium dioxide and water.

Questions or Comments

Call 1-855-314-1850

PACKAGE LABEL.PRINCIPAL DISPLAY PANEL

DIPHENHYDRAMINE HYDROCHLORIDE SOFTGEL CAPSULE, USP 50 MG

NDC:76168-065-37 16 Softgel Liquid filled